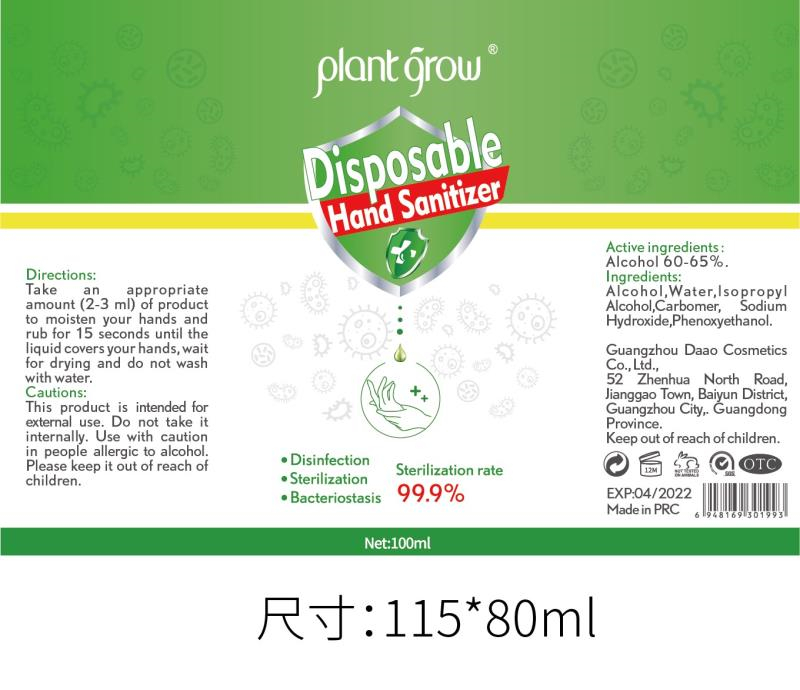 DRUG LABEL: disposable hand sanitizer
NDC: 52965-005 | Form: LIQUID
Manufacturer: Guangzhou Da'ao Cosmetics Co., Ltd
Category: otc | Type: HUMAN OTC DRUG LABEL
Date: 20200510

ACTIVE INGREDIENTS: ALCOHOL 61 mL/100 mL; ISOPROPYL ALCOHOL 6 mL/100 mL
INACTIVE INGREDIENTS: TROLAMINE; WATER; CARBOMER HOMOPOLYMER, UNSPECIFIED TYPE

ACTIVE INGREDIENT

ALCOHOL,ISOPROPANOL

PURPOSE

Disinfe ction
Sterilization
No Rinseing

INACTIVE INGREDIENT

WATER,CARBOMER,TRIETHANOLAMINE

keep out of reach of children

WARNINGS

This product is intended for external use. Do not take it internally. Use with caution in people allergic to alcohol.Please keep it out of reach of children.

DOSAGE AND ADMINISTRATION

Flammable keep away from fire or flame

INDICATIONS AND USAGE

take an appropriate amount(2-3ml) of product to moisten your hands and rub for 15 seconds until the liquid covers your hands, wait for drying and do not wash with water.